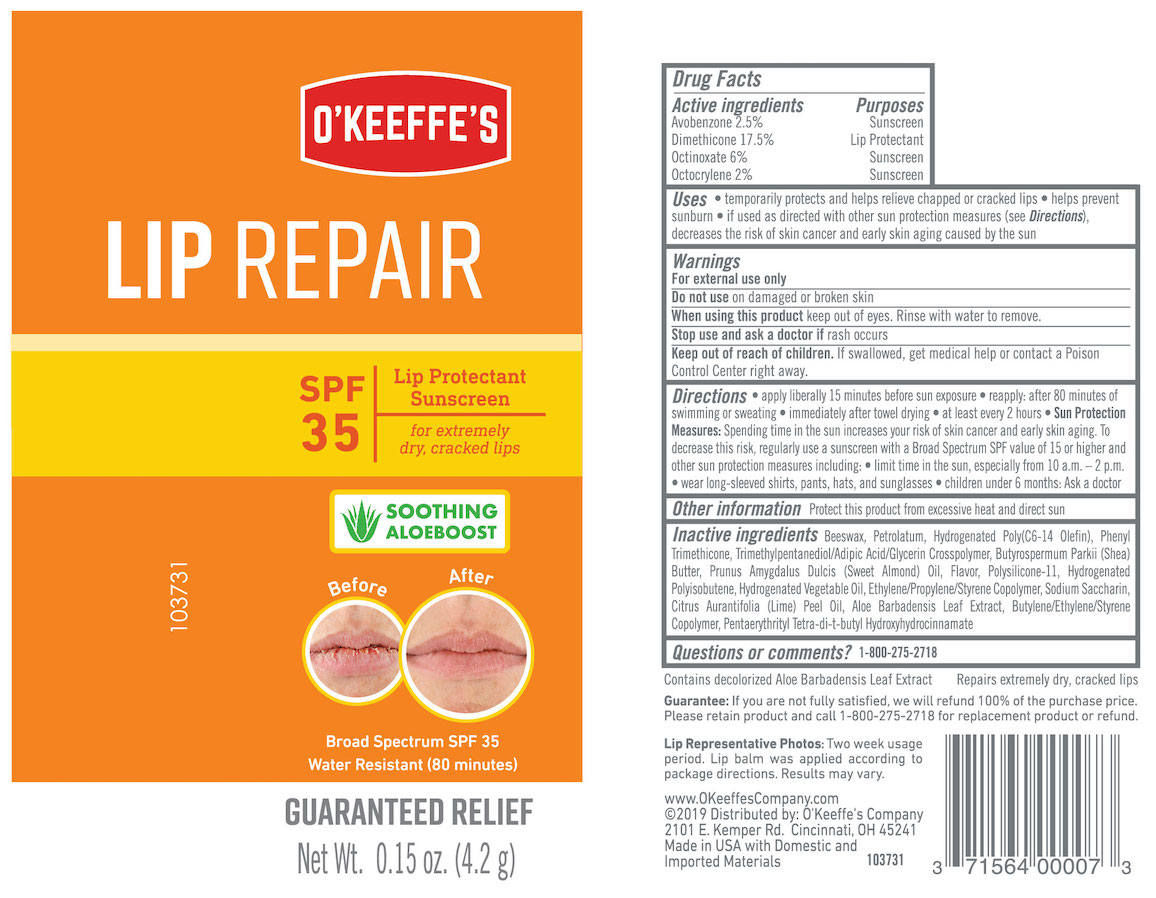 DRUG LABEL: OKeeffes Lip Repair
NDC: 71564-001 | Form: STICK
Manufacturer: The Gorilla Glue Company/O'Keeffe's Company
Category: otc | Type: HUMAN OTC DRUG LABEL
Date: 20260101

ACTIVE INGREDIENTS: AVOBENZONE 2.5 g/100 g; DIMETHICONE 17.5 g/100 g; OCTINOXATE 6 g/100 g; OCTOCRYLENE 2 g/100 g
INACTIVE INGREDIENTS: SHEA BUTTER; DIMETHICONE/VINYL DIMETHICONE CROSSPOLYMER (SOFT PARTICLE); CORN OIL; HYDROGENATED POLYBUTENE (1300 MW); SACCHARIN SODIUM; ALOE VERA LEAF; HYDROGENATED POLY(C6-14 OLEFIN; 2 CST); LIME OIL; PENTAERYTHRITOL TETRAKIS(3-(3,5-DI-TERT-BUTYL-4-HYDROXYPHENYL)PROPIONATE); YELLOW WAX; PETROLATUM; PHENYL TRIMETHICONE; TRIMETHYLPENTANEDIOL/ADIPIC ACID/GLYCERIN CROSSPOLYMER (25000 MPA.S); ALMOND OIL

O'KEEFFE'S LIP REPAIR SPF 35 STICK

Drug Facts

Active ingredients

Avobenzone 2.5%

Dimethicone 17.5%

Octinoxate 6%

Octocrylene 2%

Purposes

Sunscreen

Lip Protectant

Sunscreen

Sunscreen

Uses

- temporarily protects and helps relieve chapped or cracked lips
- helps prevent sunburn
- if used as directed with other sun protection measures (see Directions), decreases the risk of skin cancer and early skin aging caused by the sun

Warnings

For external use only

Do not use on damaged or broken skin

When using this product keep out of eyes. Rinse with water to remove.

Stop use and ask a doctor if rash occurs

Keep out of reach of children. If swallowed, get medical help or contact a Poison Control Center right away.

Directions

- apply liberally 15 minutes before sun exposure
- reapply: after 80 minutes of swimming or sweating
- immediately after towel drying
- at least every 2 hours
- Sun Protection Measures: Spending time in the sun increases your risk of skin cancer and early skin aging. To decrease this risk, regularly use a sunscreen with a Broad Spectrum SPF value of 15 or higher and other sun protection measures including:
- limit time in the sun, especially from 10 a.m. - 2 p.m.
- wear long-sleeved shirts, pants, hats and sunglasses
- children under 6 months: ask a doctor

Other information Protect this product from excessive heat and direct sun

INACTIVE INGREDIENT

Inactive ingredients Beeswax, Petrolatum, Hydrogenated Poly (C6-14 Olefin), Phenyl Trimethicone, Trimethylpentanediol/Adipic Acid/Glycerin Crosspolymer, Butyrospermum Parkii (Shea) Butter, Prunus Amygdalus Dulcis (Sweet Almond) Oil, Flavor, Polysilicone-11, Hydrogenated Polyisobutane, Hydrogenated Vegetable Oil, Ethylene/Propylene/Styrene Copolymer, Sodium Saccharin, Citrus Aurantifolia (Lime) Peel Oil, Aloe Barbadensis Leaf Extract, Butylene/Ethylene/Styrene Copolymer, Pentaerythrityl Tetra-di-t-butyl Hydroxyhydrocinnamate

Questions or comments? 1-800-275-2718

Contains decolorized Aloe Barbadensis Leaf Extract

Repairs extremely dry, cracked lips

100% Money Back Guarantee: If you are not fully satisfied with the performance of this product, we will refund 100% of the purchase price. For a prompt refund, simply return the unused portion of this product and your receipt to: O'Keeffe's Company.

LIP REPRESENTATIVE PHOTOS: Two week usage period. Lip balm was applied according to package directions. Results may vary.

www.OKeeffesCompany.com

©2019 Distributed by: O'Keeffe's Company

2101 E. Kemper Rd. Cincinnati, OH 45241

Made in USA with Domestic and Imported Materials

PACKAGE LABEL

O'KEEFFE'S LIP REPAIR

SPF 35

Lip Protectant

Sunscreen

for extremely dry, cracked lips

SOOTHING ALOE BOOST

Broad Spectrum SPF 35

Water Resistant (80 minutes)

GUARANTEED RELIEF

Net Wt. 0.15 oz. (4.2 g)